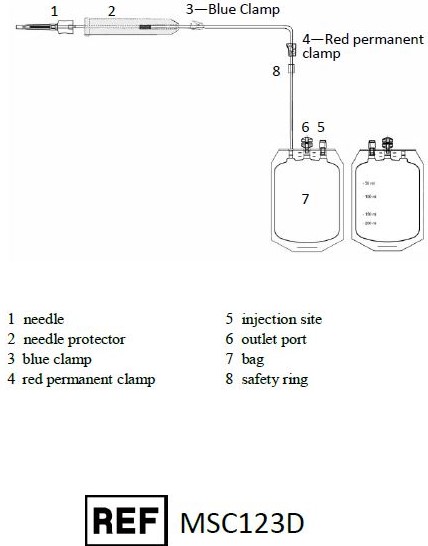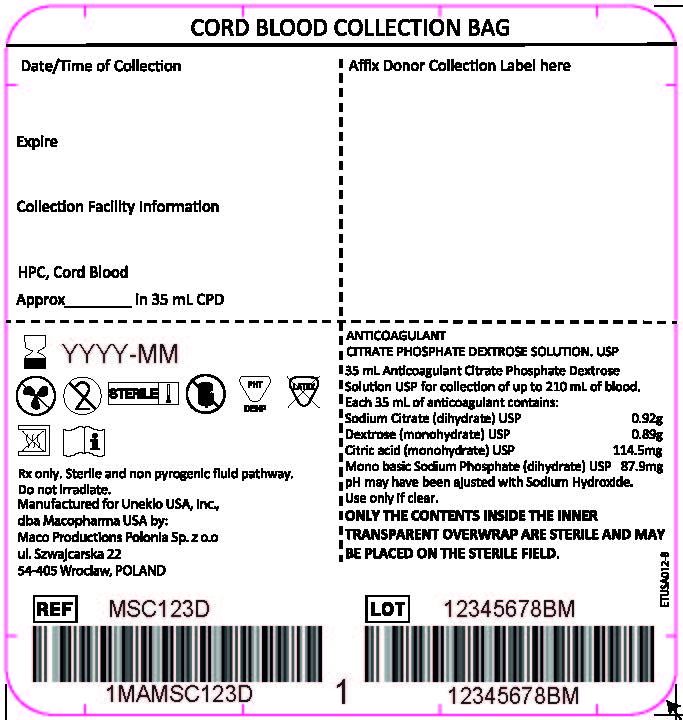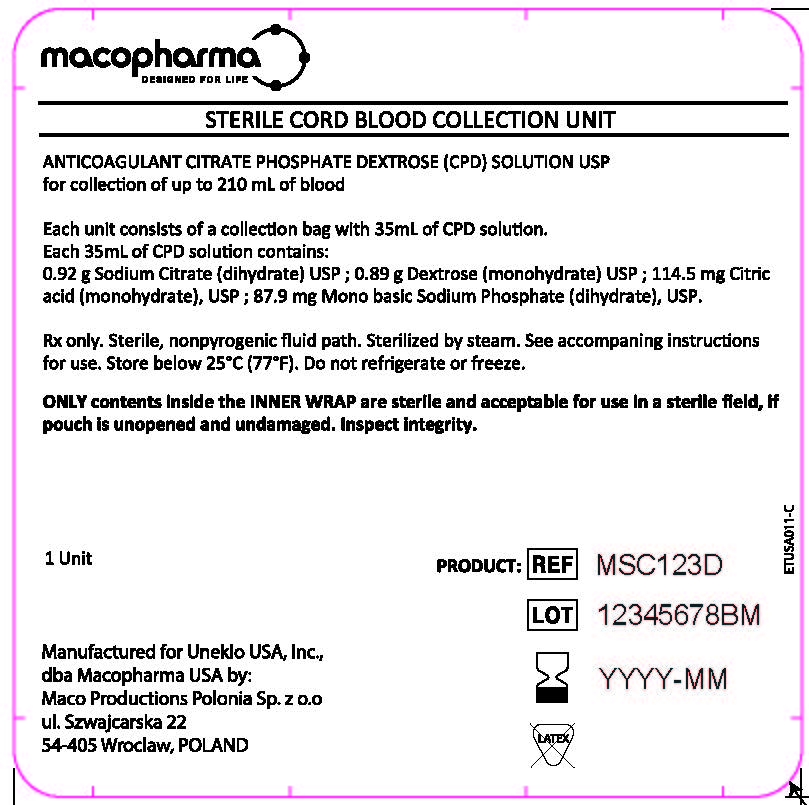 DRUG LABEL: STERILE CORD BLOOD COLLECTION UNIT (MSC123D)
NDC: 14498-005 | Form: INJECTION, SOLUTION
Manufacturer: Maco Productions
Category: prescription | Type: HUMAN PRESCRIPTION DRUG LABEL
Date: 20251216

ACTIVE INGREDIENTS: SODIUM CITRATE 0.92 g/35 mL; DEXTROSE MONOHYDRATE 0.89 g/35 mL; CITRIC ACID MONOHYDRATE 114.5 g/35 mL; SODIUM PHOSPHATE, MONOBASIC, DIHYDRATE 87.9 g/35 mL

STERILE CORD BLOOD COLLECTION UNIT (MSC123D)

MACO BIOTECH Collection- Sterile Cord Blood Collection Unit (MSC123D)

The MSC123D Sterile Cord Blood Collection Unit consists of 250 mL collection bag containing 35 mL of Anticoagulant Citrate Phosphate Dextrose Solution USP (CPD) and one 12 gauge needle with a protective shield (SECUVAM) for the used needle. Sterile, non-pyrogenic fluid path. Sterilized by steam.
Rx only.
This product is not made with natural rubber latex.

INDICATIONS AND USAGE

MSC123D - For collection of up to 210 mL of umbilical cord blood. Use aseptic technique.

WARNINGS

- Avoid contact with sharp objects.
- Do not irradiate collected cord blood or components.
- Making multiple punctures of the umbilical cord to increase collection volume may increase the risk of contamination.

PRECAUTIONS

- The kit within its aluminum outer overwrap must be stored at room temperature and protected from freezing: do not refrigerate or freeze.
- DO NOT use if the overwraps or bags show any signs of alteration.
- This is a single use sterile kit: under no circumstances should it be reused.
- For optimal cord blood quality it is recommended to maintain the cord blood at an ambient temperature (18-26°C / 64.4-78.8°F) or cold temperature (4-2°C / 39.2-53.6°F) and process within 48 hours of collection.^1,2,3.

If the collection volume is less than 60 mL, the cord blood should be processed within 24 hours of collection.

HOW SUPPLIED

MSC123D Sterile Cord Blood Collection Unit contains:

- 250 mL collection bag containing 35 mL CPD
- 1– 12 gauge needle with a protective shield (SECUVAM) for used needle
- Printed volume indications as visual aid to approximate the volume.

INSTRUCTIONS FOR USE

Carefully Read All the Instructions Before Use

Representative Product Drawing

I. PREPARATION

1. Before use, verify the integrity of the collection unit (overwrap, outlet ports, tubing…).
2. Only contents inside the inner wrap are sterile and acceptable for use in a sterile field if pouch is unopened and undamaged.

II. COLLECTION PROCEDURE

1. Close the clamp 3 (clamp 4 should remain open).
2. After clamping and sectioning of the umbilical cord, place the collection bag on a mixer and perform a venipuncture at lower end of the umbilical cord with needle 1. Note: Umbilical venipunctures can be done before or after the expulsion of the placenta according to your local procedures.
3. Open clamp 3.
4. Stimulate cord blood flow by massaging the cord from the top downward to increase volume of collection.
5. When collection is completed, close clamp 3.
6. Remove needle 1 and slide down SECUVAM 2 (needle protector) over needle 1.

III. ADDITION OF CORD BLOOD FROM THE TUBE TO THE SAMPLING POUCH

1. Move clamp 3 at the top of the collection line close to the needle protector 2
2. Using a blood stripper, strip the tubing from the top of the tube towards the safety ring expelling the blood in the tubing into collection bag 7.
3. Repeat this operation 3 times.
4. Mix collection bag 7.
5. Close clamp 3.

IV. END OF COLLECTION

1. Close clamp 4 to secure the collection above the safety ring 8.
2. Seal the tubing above the clamp 4.
3. Fill in collection volume on the collection bag label.
4. For optimal cord blood quality, maintain the cord blood at an ambient temperature (18-26°C / 64.4-78.8°F) or cold temperature (4-12°C / 39.2-53.6°F) and process within 48 hours of collection.^1,2,3

If the collection volume is less than 60 mL, the cord blood should be processed within 24 hours of collection.

VI. CONTACT INFORMATION

Manufactured for United States of America (U.S.A.) by Maco Productions Polonia, Sp. z o.o. ul. Szwajcarska 22, 54-405 Wroclaw, POLAND +48 71 37 60 110
For consumer information contact:
Distributed by Uneklo USA, Inc., dba Macopharma USA, 3075 Breckinridge Boulevard, Suite 405, Duluth, GA 30096, USA (770) 270-6867

VII. REFERENCES

1. Pope, B., Mitsakos, K., Bilgin, A., Hokin, B. and Grant, R: Predicting overall viability of cord blood harvests. Transfusion 2012; 52:1079-1085
2. Salge-Bartels U. Huber. M, Kleiner K, Volkers P, Seitz R, Heiden M: Evaluation of Quality Parameters for Cord Blood Donations, Transfus Med Hemother 2009; 36:317-324
3. Prof. Dr.Kogler, Jose Carreras CBB, medical Center, University of Duesseldorf : General information on the institution and the production facility of the Jose Carreras Cord Blood Bank. 2014

PRINCIPAL DISPLAY PANEL

LABELS

Collection Bag Label

Overwrap Label